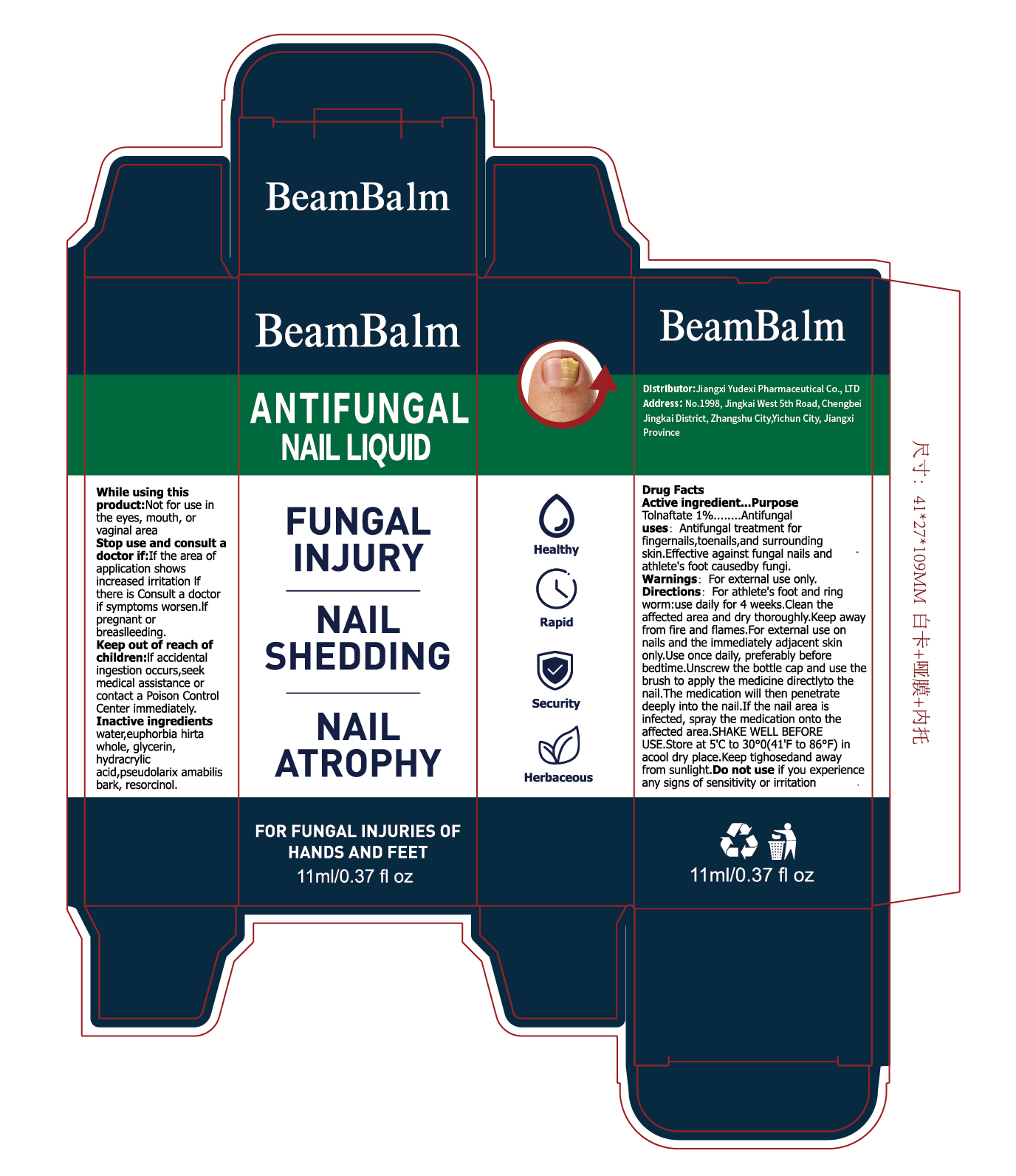 DRUG LABEL: BeamBalm  ANTIFUNGAL NAIL
NDC: 85248-048 | Form: LIQUID
Manufacturer: Jiangxi Yudexi Pharmaceutical Co., LTD
Category: otc | Type: HUMAN OTC DRUG LABEL
Date: 20260204

ACTIVE INGREDIENTS: TOLNAFTATE 1 g/100 mL
INACTIVE INGREDIENTS: EUPHORBIA HIRTA WHOLE; WATER; HYDRACRYLIC ACID; PSEUDOLARIX AMABILIS BARK; RESORCINOL; GLYCERIN

85248-048

Active Ingredient

Tolnaftate 1%

Purpose

Antifungal

Use

Antifungal treatment for fingernails,toenails, and surrounding skin.Effective against fungal nails and athlete's foot caused by fungi.

Warnings

For external use only.

Do not use

if you experience any signs of sensitivity or irritation

When Using

Not for use in the eyes, mouthor vaginal area.

Stop Use

lf the area of application shows increased irritation lf there is Consult a doctor if symptoms worsen.If pregnant or breaslleeding

Ask Doctor

lf the area of application shows increased irritation lf there is Consult a doctor if symptoms worsen.If pregnant or breaslleeding

Keep Oot Of Reach Of Children

lf accidental ingestion occurs,seek medical assistance or contact a Poison Control Center immediately.

Directions

For athlete's foot and ringworm：use daily for 4 weeks.Clean the affected area and dry thoroughly.Keep away from fire and flames.For external use on nails and the immediately adjacent skin only.Use once daily, preferably before bedtime.
Unscrew the bottle cap and use the brush to apply the medicine directlyto the nail.The medication will then penetrate deeply into the nail.If the nail area is infected, spray the medication onto the affected area.SHAKE WELL BEFORE USE.Store at 5℃ to 30℃(41ºF to 86°F) in a cool dry place. Keep tighosedand away from sunlight.

Inactive ingredients

water ,euphorbia hirta whole, glycerin hydracrylic acid, pseudolarix amabilis bark, resorcinol.